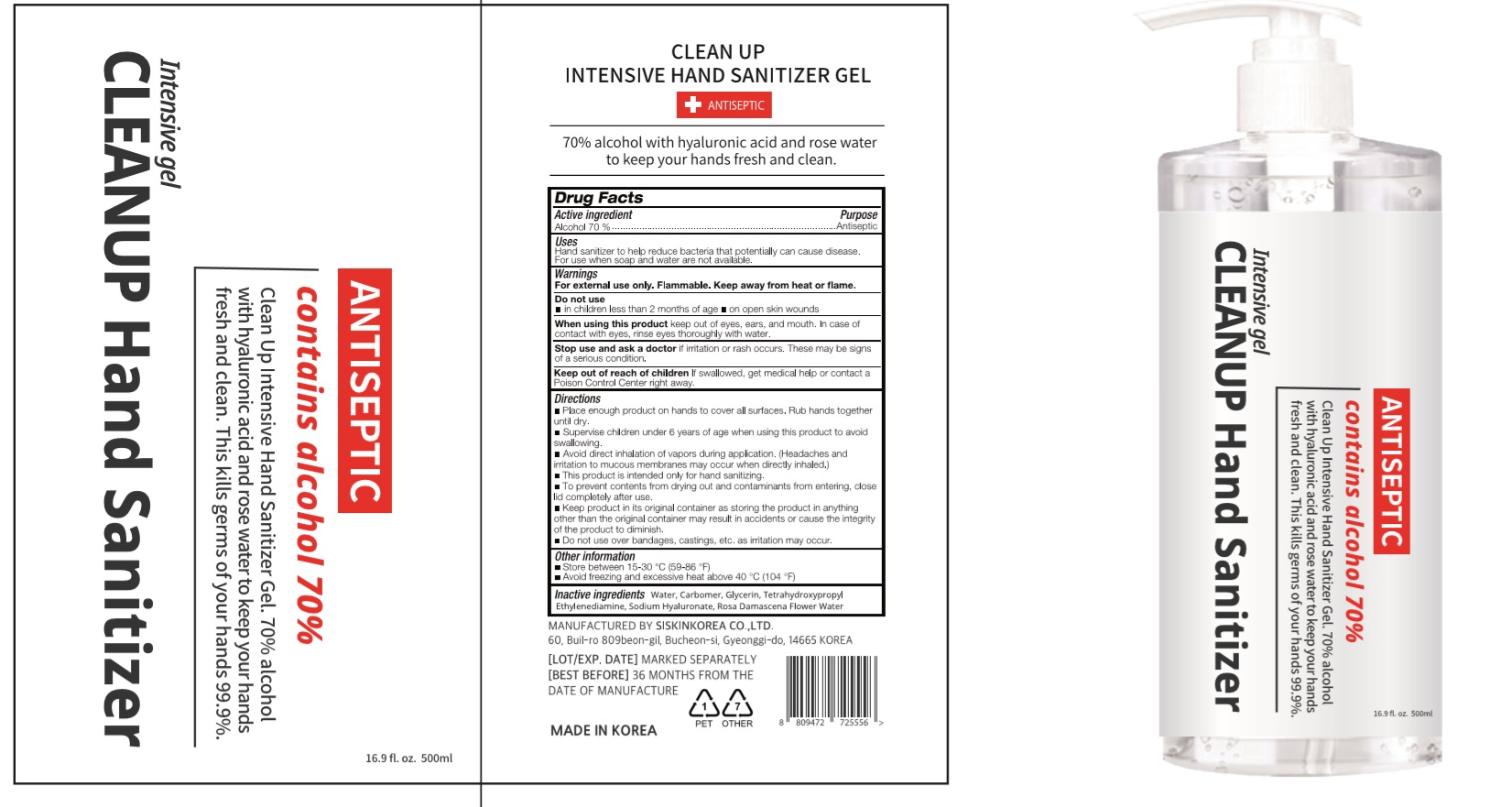 DRUG LABEL: CLEAN UP Intensive Hand Sanitizer Gel
NDC: 74514-3004 | Form: GEL
Manufacturer: SISKINKOREA CO.,LTD.
Category: otc | Type: HUMAN OTC DRUG LABEL
Date: 20200626

ACTIVE INGREDIENTS: ALCOHOL 350 mL/500 mL
INACTIVE INGREDIENTS: GLYCERIN; ROSA DAMASCENA FLOWER OIL; EDETOL; WATER; HYALURONATE SODIUM; CARBOMER HOMOPOLYMER, UNSPECIFIED TYPE

CLEAN UP Intensive Hand Sanitizer Gel | 500 mL | 74514-3004-1